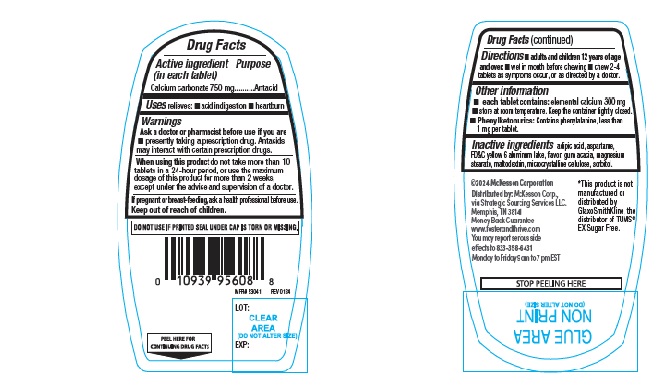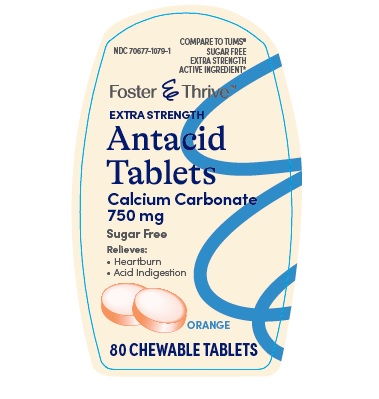 DRUG LABEL: Foster and Thrive Extra Strength Sugar Free Antacid Orange
NDC: 70677-1079 | Form: TABLET, CHEWABLE
Manufacturer: Strategic Sourcing Services LLC
Category: otc | Type: Human OTC Drug Label
Date: 20240221

ACTIVE INGREDIENTS: CALCIUM CARBONATE 750 mg/1 1
INACTIVE INGREDIENTS: ADIPIC ACID; ASPARTAME; FD&C YELLOW NO. 6; MAGNESIUM STEARATE; MALTODEXTRIN; CELLULOSE, MICROCRYSTALLINE; SORBITOL; ACACIA

Foster and Thrive Extra Strength Antacid Sugar Free Orange Chewable 174

ACTIVE INGREDIENT(S)

Calcium carbonate 750 mg

PURPOSE

Antacid

USE(S)

relieves:

- acid indigestion
- heartburn

WARNINGS

.

ASK A DOCTOR OR PHARMACIST BEFORE USE IF YOU ARE

- presently taking a prescription drug. Antacids may interact with certain prescription drugs.

WHEN USING THIS PRODUCT

do not take more than 10 tablets in a 24-hour period, or use the maximum dosage of this product for more than 2 weeks, except under the advice and supervision of a doctor.

IF PREGNANCY OR BREAST-FEEDING,

ask a health professional before use.

KEEP OUT OF REACH OF CHILDREN

.

DIRECTIONS

- adults and children 12 years of age and over:
- wet in mouth before chewing
- chew 2-4 tablets as symptoms occur, or as directed by a doctor.

OTHER INFORMATION

- each tablet contains: elemental calcium 300 mg
- Phenylketonurics: Contains phenylalanine, less than 1 mg per tablet.
- store below 30o c(86o F).

INACTIVE INGRADIENTS

adipic acid, aspartame, FD&C yellow 6 aluminum lake, flavor, gum acacia, magnesium stearate, maltodextrin, microcrystalline cellulose, sorbitol.

PRINCIPAL DISPLAY PANEL

NDC 70677-1079-1

COMPARE TO TUMS® SUGAR FREE

EXTRA STRENGTH ACTIVE INGREDIENT*

Foster & Thrive TM

EXTRA STRENGTH

Antacid Tablets

Calcium Carbonate 750mg

Sugar Free

Relieves:

- Heartburn
- Acid Indigestion

ORANGE

80 CHEWABLE TABLETS